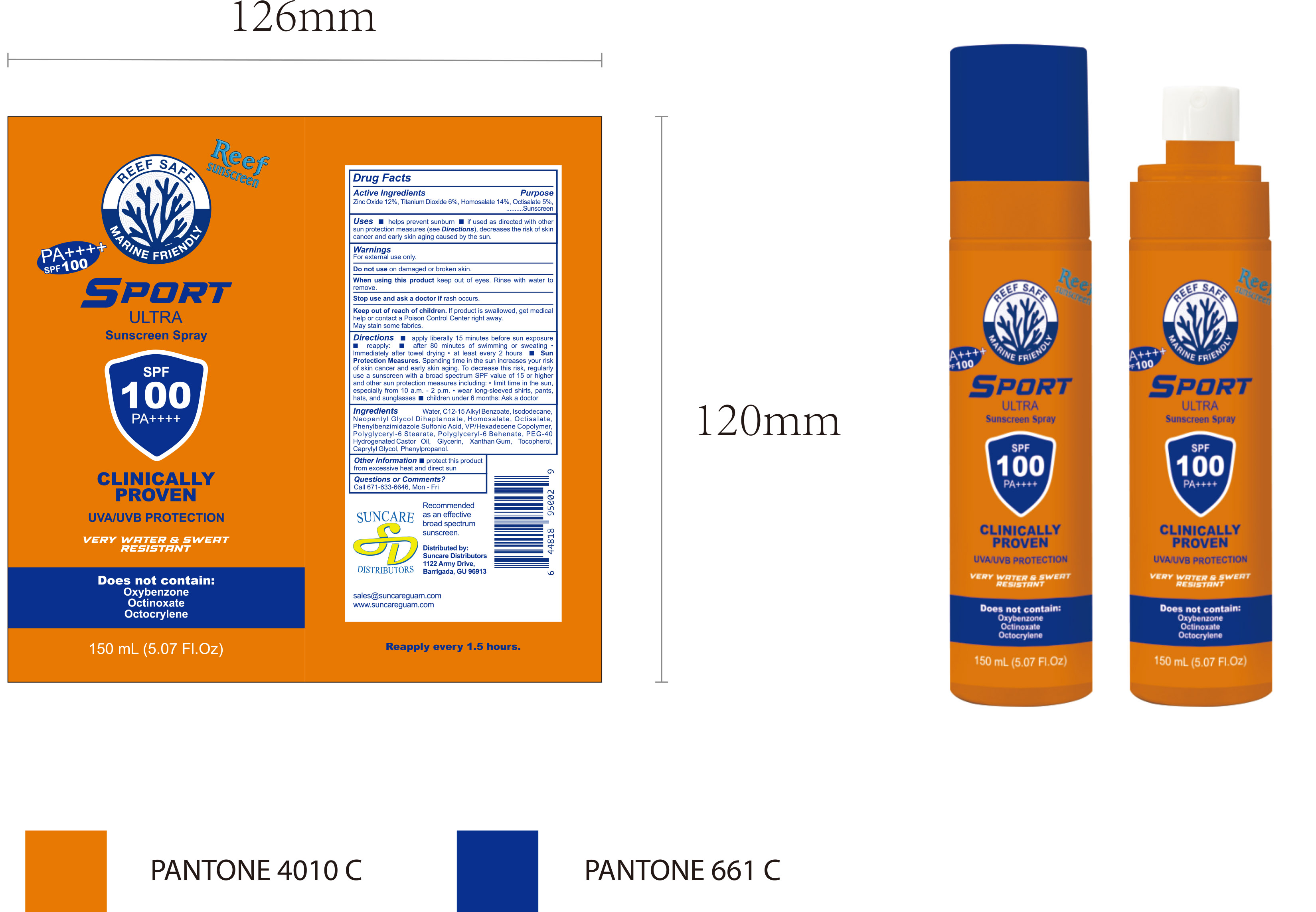 DRUG LABEL: SUNSCREEN SPRAY150mL
NDC: 84938-014 | Form: LIQUID
Manufacturer: Foshan Sugar Max Cosmetics CO.,Ltd
Category: otc | Type: HUMAN OTC DRUG LABEL
Date: 20251218

ACTIVE INGREDIENTS: HOMOSALATE 0.14 g/1 mL; ZINC OXIDE 0.12 g/1 mL; TITANIUM DIOXIDE 0.06 g/1 mL; OCTISALATE 0.05 g/1 mL
INACTIVE INGREDIENTS: VP/HEXADECENE COPOLYMER; POLYGLYCERYL-6 STEARATE; XANTHAN GUM; PHENYLBENZIMIDAZOLE SULFONIC ACID; NEOPENTYL GLYCOL DIHEPTANOATE; AQUA; PEG-40 HYDROGENATED CASTOR OIL; PHENYLPROPANOL; ISODODECANE; POLYGLYCERYL-6 BEHENATE; CAPRYLYL GLYCOL; ALKYL (C12-15) BENZOATE; GLYCERIN; TOCOPHEROL

84938-014 SUNSCREEN SPRAY

ACTIVE INGREDIENT

Zinc Oxide 12%, Titanium Dioxide 6%, Homosalate14%, Octisalate 5%

PURPOSE

Sunscreen

INDICATIONS AND USAGE

Uses helps prevent sunburn if used as directed with other sun protection measures (see Directions), decreases the risk of skin cancer and early skin aging caused by the sun.

WARNINGS

For external use only.

Do not use on damaged or broken skin

When using this product keep out of eyes. Rinse with water to remove.

Stop use and ask a doctor if rash occurs

Keep out of reach of children. lf product is swallowed, get medical help or contact a Poison Control Center right away. May stain some fabrics.

DOSAGE AND ADMINISTRATION

Directions apply liberally 15 minutes before sun exposure reapply: after 80 minutes of swimming or sweating Immediately after towel drying "at least every 2 hours SunProtection Measures. Spending time in the sun increases your risk of skin cancer and early skin aging. To decrease this risk, regularly use a sunscreen with a broad spectrum SPF value of 15 or higher and other sun protection measures including: " limit time in the sun,especially from 10 a.m.-2 p.m.·wear long-sleeved shirts, pants hats, and sunglasses

children under 6 months: Ask a doctor

INACTIVE INGREDIENT

Aqua (Water)
C12‑15 Alkyl Benzoate
Isododecane
Neopentyl Glycol Diheptanoate
Phenylbenzimidazole Sulfonic Acid (Ensulizole)
VP/Hexadecene Copolymer
Polyglyceryl‑6 Stearate
Polyglyceryl‑6 Behenate
PEG‑40 Hydrogenated Castor Oil
Glycerin
Xanthan Gum
Tocopherol (Vitamin E)
Caprylyl Glycol
Phenylpropanol